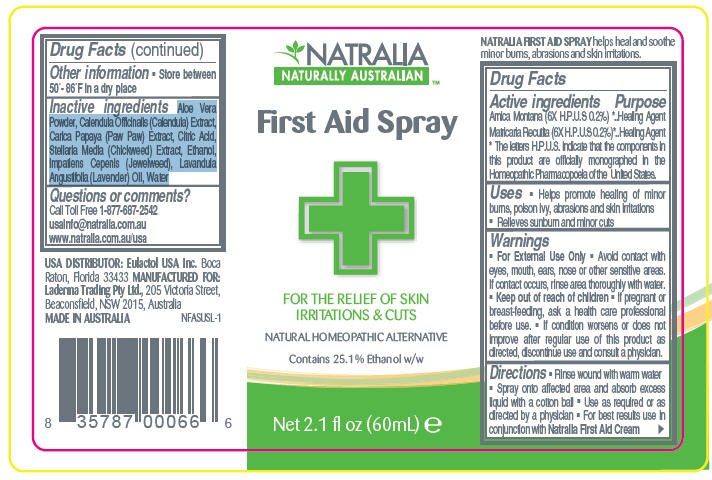 DRUG LABEL: FLEXITOL FIRST AID
NDC: 43251-3353 | Form: SPRAY
Manufacturer: Laderma Trading Pty Ltd
Category: otc | Type: HUMAN OTC DRUG LABEL
Date: 20100129

ACTIVE INGREDIENTS: ARNICA MONTANA FLOWER 2 mg/1 mL; CHAMOMILE 2 mg/1 mL

NATRALIA
NATURALLY AUSTRALIAN ™
First Aid Spray

Drug Facts

ACTIVE INGREDIENT

Active ingredients | Purpose
Arnica Montana (6X H.P.U.S 0.2%) [The letters H.P.U.S. indicate that the components in this product are officially monographed in the Homeopathic Pharmacopoeia of the United States.] | Healing Agent
Matricaria Recutita (6X H.P.U.S 0.2%) | Healing Agent

Uses

- Helps promote healing of minor burns, poison ivy, abrasions and skin irritations
- Relieves sunburn and minor cuts

Warnings

- For External Use Only
- Avoid contact with eyes, mouth, ears, nose or other sensitive areas. If contact occurs, rinse area thoroughly with water.
- Keep out of reach of children
- If pregnant or breast-feeding, ask a health care professional before use.
- If condition worsens or does not improve after regular use of this product as directed, discontinue use and consult a physician.

Directions

- Rinse wound with warm water
- Spray onto affected area and absorb excess liquid with a cotton ball
- Use as required or as directed by a physician
- For best results use in conjunction with Natralia First Aid Cream

Other information

- Store between 50°- 86°F in a dry place

Inactive ingredients

Aloe Vera Powder, Calendula Officinalis (Calendula) Extract, Carica Papaya (Paw Paw) Extract, Citric Acid, Stellaria Media (Chickweed) Extract, Ethanol, Impatiens Cepenis (Jewelweed), Lavandula Angustifolia (Lavender) Oil, Water

Questions or comments?

Call Toll Free 1-877-687-2542
usainfo@natralia.com.au
www.natralia.com.au/usa

Principal Display Panel - 2.1 fl oz Label

NATRALIA
NATURALLY AUSTRALIAN™

First Aid Spray

FOR THE RELIEF OF SKIN
IRRITATIONS & CUTS

NATURAL HOMEOPATHIC ALTERNATIVE

Contains 25.1% Ethanol w/w

Net 2.1 fl oz (60mL) e